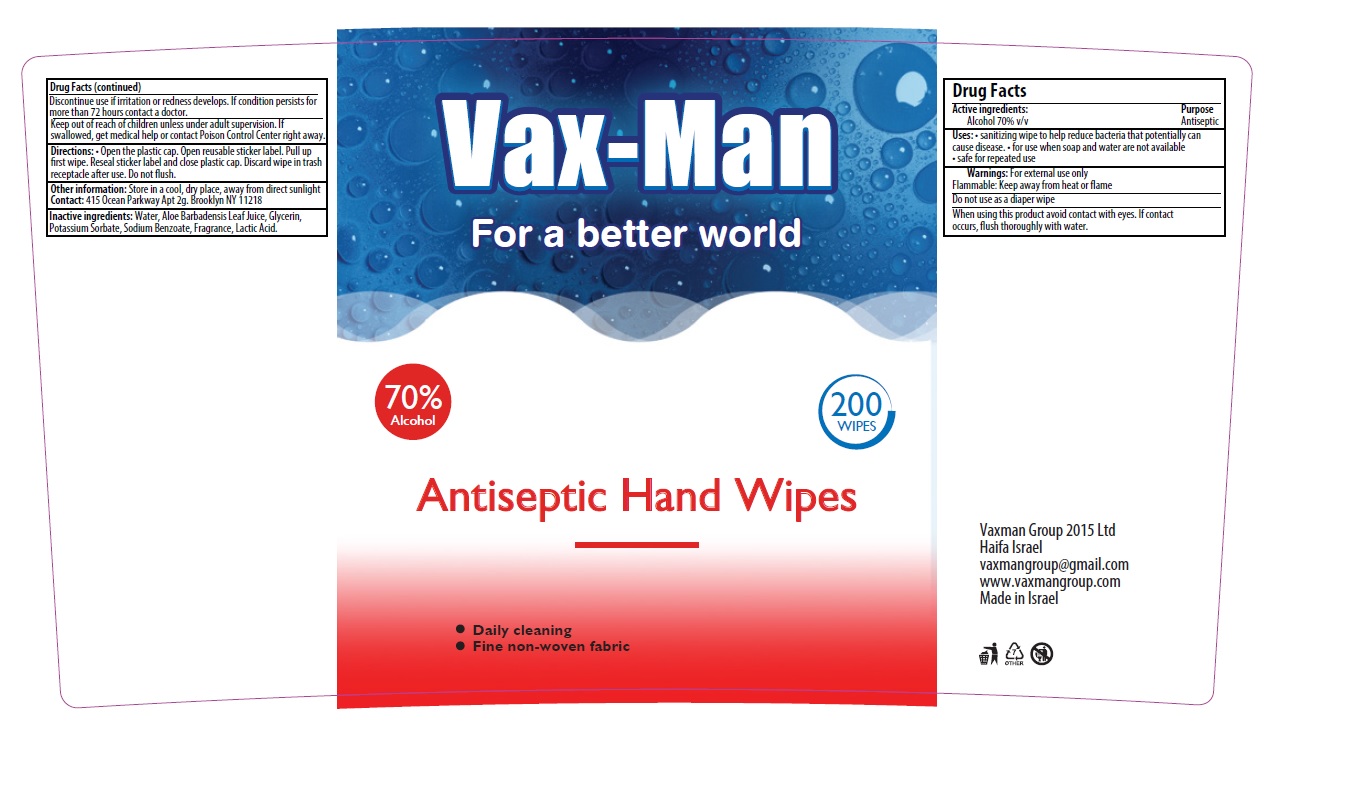 DRUG LABEL: VAX-MAN ANTISEPTIC HAND WIPES
NDC: 79566-001 | Form: CLOTH
Manufacturer: Vaxman Group 2015 Ltd.
Category: otc | Type: HUMAN OTC DRUG LABEL
Date: 20200710

ACTIVE INGREDIENTS: ALCOHOL 70 mL/100 mL
INACTIVE INGREDIENTS: ALOE VERA LEAF; GLYCERIN; WATER; POTASSIUM SORBATE; SODIUM BENZOATE; LACTIC ACID

Vax-Man Antiseptic Hand Wipes

Active ingredients

Alcohol 70% v/v

Purpose

Antiseptic

Uses

- sanitizing wipe to help reduce bacteria that potentially can cause disease
- for use when soap and water are not available
- safe for repeated use

Warnings

For external use only.

Flammable. Keep away from heat or flame.

Do not use

as a diaper wipe

When using this product

avoid contact with eyes. If contact occurs, flush thoroughly with water.

Discontinue use

if irritation or redness develops. If condition persists for more than 72 hours contact a doctor.

Keep out of reach of children

unless under adult supervision. If swallowed, get medical help or contact a Poison Control Center right away.

Directions

- Open the plastic cap. Open reusable sticker label. Pull up first wipe. Reseal sticker label and close plastic cap. Discard wipe in trash receptacle after use. Do not flush.

Other information

Store in a cool, dry place, away from direct sunlight

Contact: 415 Ocean Parkway Apt 2g. Brooklyn NY 11218

Inactive ingredients

Water, Aloe Barbadensis Leaf Juice, Glycerin, Potassium Sorbate, Sodium Benzoate, Fragrance, Lactic Acid.

Company Information

Vaxman Group 2015 Ltd

Haifa Israel

vaxmangroup@gmail.com

www.vaxmangroupcom

Made in Israel

Product Packaging - 200 wipe canister

Vax-Man

Antiseptic Hand Wipes

For a better world

70% Alcohol

200 WIPES